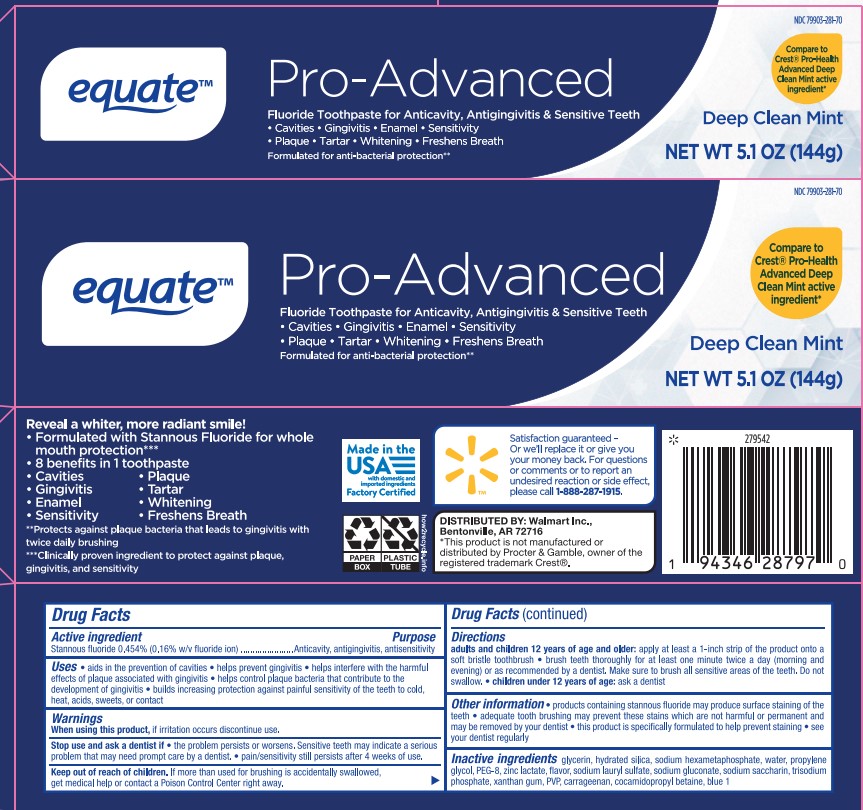 DRUG LABEL: Equate Pro-Advanced TP
NDC: 79903-281 | Form: PASTE, DENTIFRICE
Manufacturer: Walmart Inc.
Category: otc | Type: HUMAN OTC DRUG LABEL
Date: 20251113

ACTIVE INGREDIENTS: STANNOUS FLUORIDE 0.16 g/100 g
INACTIVE INGREDIENTS: SACCHARIN SODIUM; ZINC LACTATE; GLYCERIN; POLYETHYLENE GLYCOL 300; XANTHAN GUM; FD&C BLUE NO. 1; WATER; CARRAGEENAN; HYDRATED SILICA; PROPYLENE GLYCOL; COCAMIDOPROPYL BETAINE; SODIUM LAURYL SULFATE; SODIUM POLYMETAPHOSPHATE; SODIUM PHOSPHATE, TRIBASIC, ANHYDROUS; POVIDONE; SODIUM GLUCONATE

5820078 Walmart Equate Pro-Advanced (80-15078)

ACTIVE INGREDIENT

Stannous fluoride 0.454% (0.16% w/v fluoride ion)

INACTIVE INGREDIENT

glycerin, hydrated silica, sodium hexametaphosphate, water, propylene glycol, PEG-8, zinc lactate, flavor, sodium lauryl sulfate, sodium gluconate, sodium saccharin, trisodium phosphate, xanthan gum, PVP, carrageenan, cocamidopropyl betaine, blue 1

PURPOSE

Anticavity, antigingivitis, antisensitivity

INDICATIONS AND USAGE

aids in the prevention of cavities

helps prevent gingivitis

helps interfere with the harmful effects of plaque associated with gingivitis

builds increasing protection against painful sensitivity of the teeth to cold, heat, acids, sweets, or contact

when using this product, if irritation occurs discontinue use.

Stop use and ask a dentist if if the problem persists or worsens. Sensitive teeth may indicate a serious problem that may need prompt care by a dentist. pain/sensitivty still persists after 4 weeks of use.

Keep out of reach or children.

Keep out of reach of children. If more than used for brushing is accidentally swallowed, get meedical help or contact a Poison Control Center right away.

DOSAGE AND ADMINISTRATION

Directions adults and children 12 years of age and older: apply at least a 1-inch strip of the product onto a soft bristle toothbrush • brush teeth thoroughly for at least one minute twice a day (morning and evening) or as recommended by a dentist.

Make sure to brush all sensitive areas of the teeth. Do not swallow. • children under 12 years of age: Consult a dentist